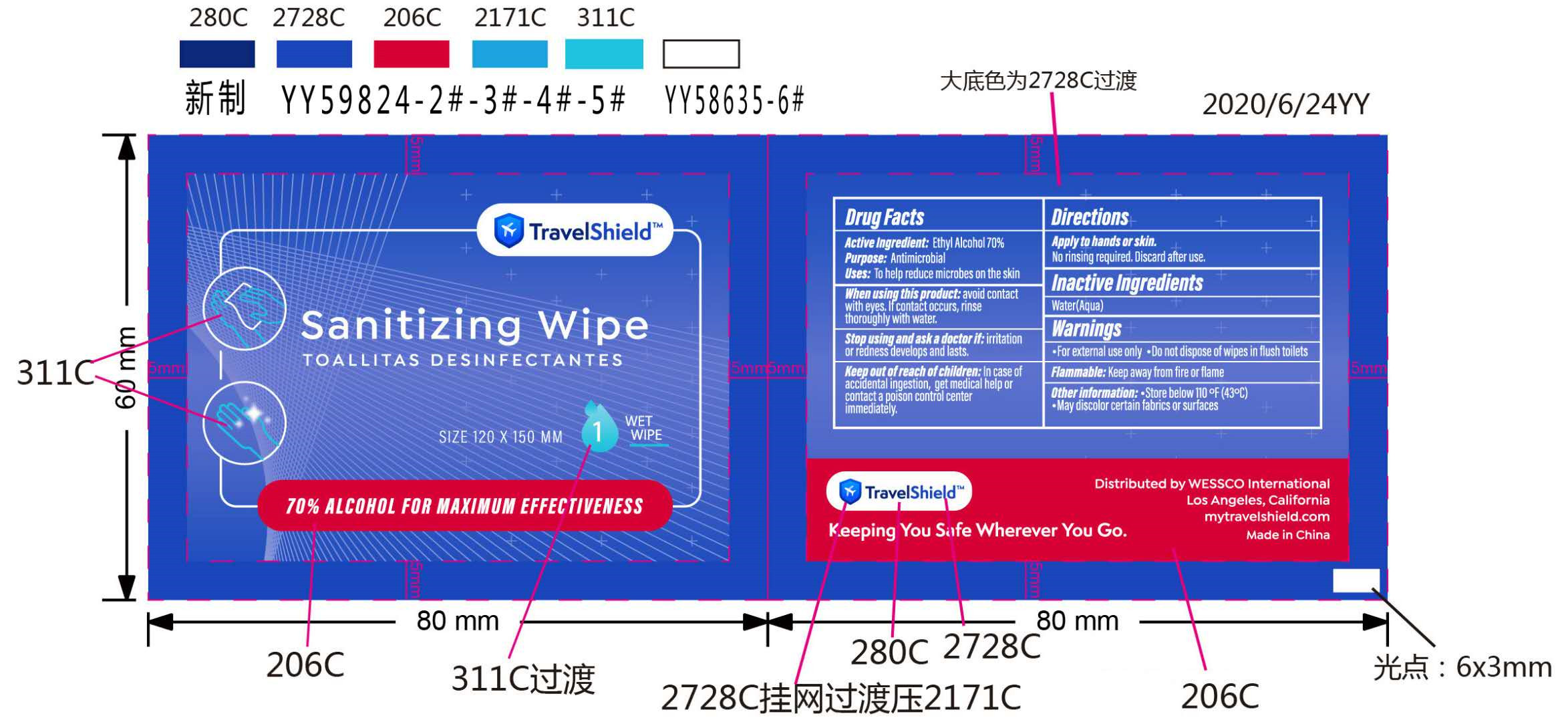 DRUG LABEL: TRAVELSHELD SANITIZING WIPE(70%Alcohol)
NDC: 96285-001 | Form: CLOTH
Manufacturer: Yangzhou Zhouwan Medical Devices Co.,Ltd
Category: otc | Type: HUMAN OTC DRUG LABEL
Date: 20201104

ACTIVE INGREDIENTS: ALCOHOL 7 mL/10 mL
INACTIVE INGREDIENTS: WATER

ACTIVE INGREDIENT

Ethyl Alcohol 70%

PURPOSE

Antimicrobial

Uses

To help reduce microbes on the skin

Directions

Apply to hands or skin.
No rinsing required.Discard after use.

WHEN USING

Avoid contactwith eyes. If contact occurs, rinse thoroughly with water.

STOP USE

irritationor redness develops and lasts.

KEEP OUT OF REACH OF CHILDREN

ln case ofaccidental ingestion,get medical help orcontact a poison control center immediately.

INACTIVE INGREDIENT

Water(Aqua)

WARNINGS

For external use only
Do not dispose of wipes in flush toilets

Keep away from fire or flame

OTHER SAFETY INFORMATION

Store below 110°F(43°C)
May discolor certain fabrics or surfaces